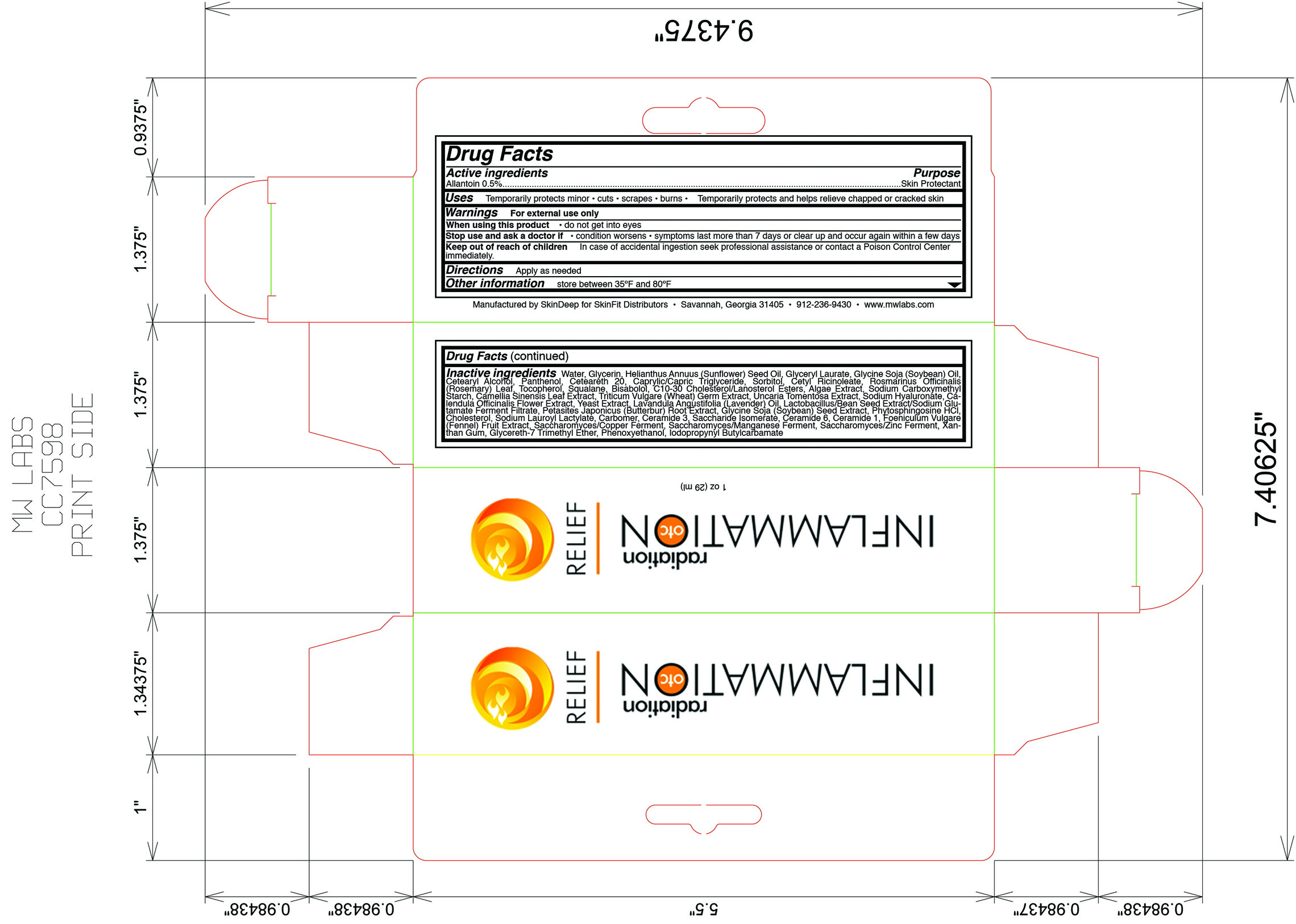 DRUG LABEL: Inflammation OTC 
NDC: 45156-5616 | Form: LOTION
Manufacturer: Skin Deep
Category: otc | Type: HUMAN OTC DRUG LABEL
Date: 20110116

ACTIVE INGREDIENTS: Allantoin 3 g/600 g
INACTIVE INGREDIENTS: Water; Glycerin; Helianthus Annuus; Glyceryl Laurate; Soybean Oil; Cetostearyl Alcohol; Dexpanthenol; Polyoxyl 20 Cetostearyl Ether; Medium-Chain Triglycerides; Sorbitol; Ricinoleic Acid; Rosemary Oil; Alpha-Tocopherol; Squalane; .Alpha.-Bisabolol, (+/-)-; Carrageenan; Sodium Starch Glycolate Type A Potato; Green Tea Leaf; Triticum Aestivum Pollen; Cat's Claw; Hyaluronate Sodium

Drug Facts

Active ingredient

Allantoin (0.5%)

Purpose

Skin protectant

Uses

Temporarily protects minor: burns, cuts, and scrapes

Temporarily protects and helps relieve

- chapped skin
- cracked skin

Warnings

For external use only

When using this product

- do not get into eyes

Keep out of reach of children

In case of accidental ingestion seek professional assistance or contact a poison control center immediately.

Directions

- Apply as needed

Stop use and ask a doctor if

- condition worsens
- symptoms last more than 7 days or clear up and occur again within a few days

Inactive ingredients

water, glycerin, helianthus annuus (sunflower) seed oil, glyceryl laurate, glycine soja (soybean) oil, cetearyl alcohol, panthenol, ceteareth 20, caprylic/capric triglyeride, sorbitol, cetyl ricinoleate, rosmarinus officinalis (rosemary) leaf, tocopherol, squalane, bisabolol, C10-30 cholesterol/lanosterol esters, algae extract,sodium carboxymethly starch, camelia sinensis leaf extract, triticum vulgare (wheat) germ extract, uncaria tomentosa extract, sodium hyaluronate, calendula officinalis flower extract, yeast extract, lavandula angustifolia (lavender) oil, lactobacillus/bean seed extract/sodium glutamate ferment filtrate, petasites japonicus (butterbur) root extract, glycine soja (soybean) seed extract, phytosphingosine HCl, cholesterol, sodium lauroyl lactylate, carbomer, ceramide 3, saccharide isomerate, ceramide 6, ceramide 1, foeniculum vulgare (fennel) fruit extract, saccharomyces/copper ferment, saccharomyces/manganese ferment, saccharomyces/zinc ferment, xanthan gum, glycereth-7 trimethyl ether, phenoxyethanol, iodopropynyl butylcarbmate

Questions or comments

call 1-912-236-9430 weekdays

Principal Display Panel

Inflammation OTC

Radiation Relief

Net wt 1 oz. (28.35 mL)

Manufactured by SkinDeep for SkinFit Distributors

Savannah, GA 31405

Tel: 912-236-9430

www.mwlabs.com